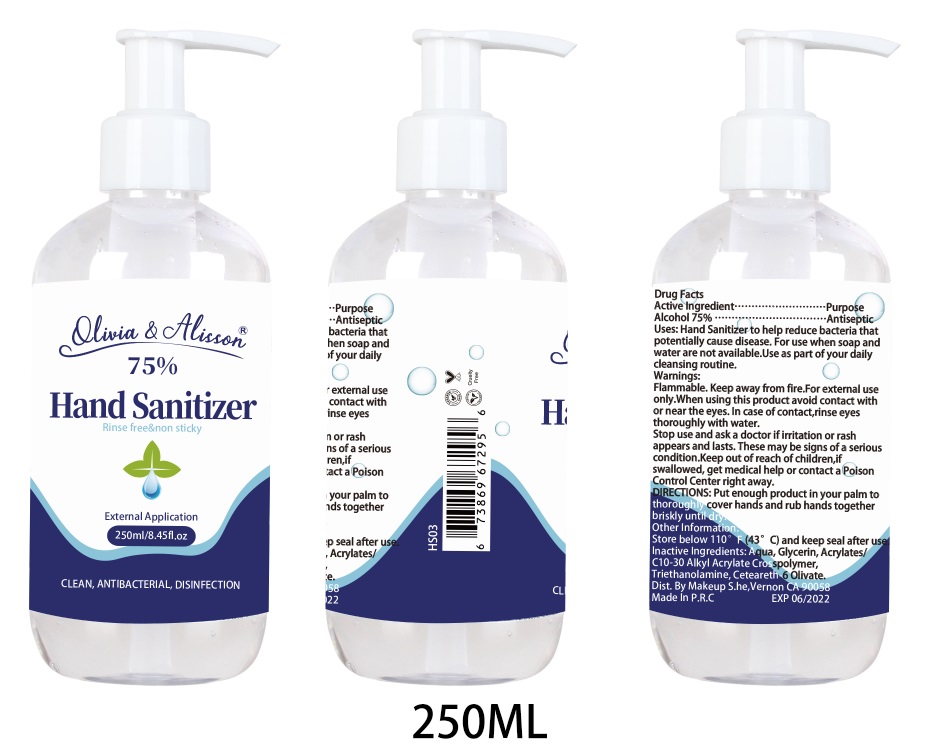 DRUG LABEL: Hand Sanitizer
NDC: 54823-007 | Form: GEL
Manufacturer: FUJIAN ISHINE COSMETICS CO., LTD.
Category: otc | Type: HUMAN OTC DRUG LABEL
Date: 20200506

ACTIVE INGREDIENTS: ALCOHOL 75 mL/100 mL
INACTIVE INGREDIENTS: CARBOMER INTERPOLYMER TYPE A (55000 CPS) 0.3 mL/100 mL; GLYCERIN 0.3 mL/100 mL; WATER 24 mL/100 mL; TROLAMINE 0.3 mL/100 mL; CETEARETH-6 OLIVATE 0.1 mL/100 mL

Hand Sanitizer

Active Ingredient

Alcohol 75%

Purpose

Antiseptic

Uses:

Hand Sanitizer to help reduce bacteria that potentially cause disease. For use when soap and water are not available.Use as part of your daily cleansing routine.

Warnings:

Flammable. Keep away from fire.For external use only.
When using this product avoid contact with or near the eyes. In case of contact,rinse eyes thoroughly with water.

Stop use and ask a doctor if irritation or rash appears and lasts. These may be signs of a serious condition.

Keep out of reach of children,if swallowed, get medical help or contact a Poison Control Center right away.

When using this product avoid contact with or near the eyes. In case of contact,rinse eyes thoroughly with water.

Stop use and ask a doctor if irritation or rash appears and lasts. These may be signs of a serious condition.

Keep out of reach of children,if swallowed, get medical help or contact a Poison Control Center right away.

DIRECTIONS:

Put enough product in your palm to thoroughly cover hands and rub hands together briskly until dry.

Other Information

Store below 110°F (43°C) and keep seal after use.

Inactive Ingredients:

Aqua, Glycerin, Acrylates/C10-30 Alkyl Acrylate Crosspolymer, Triethanolamine, Ceteareth-6 Olivate

Package Label

75%

Hand Sanitizer

Rinse free&non sticky

External Application

Net Wt:250ml / 8.45fl.oz

Clean,antibacterial,Disinfection